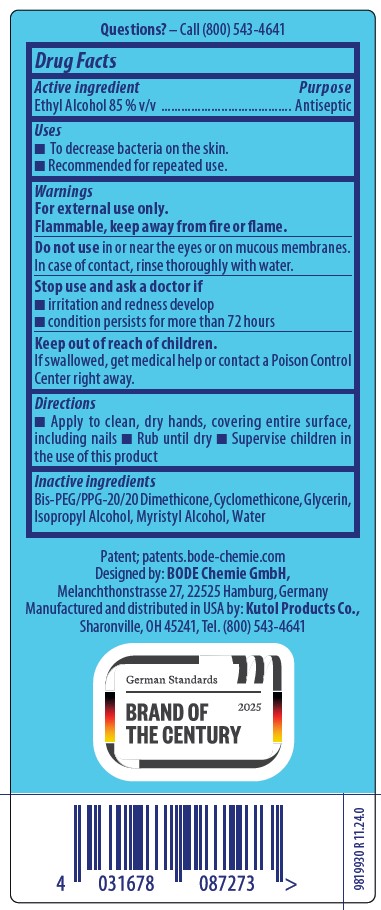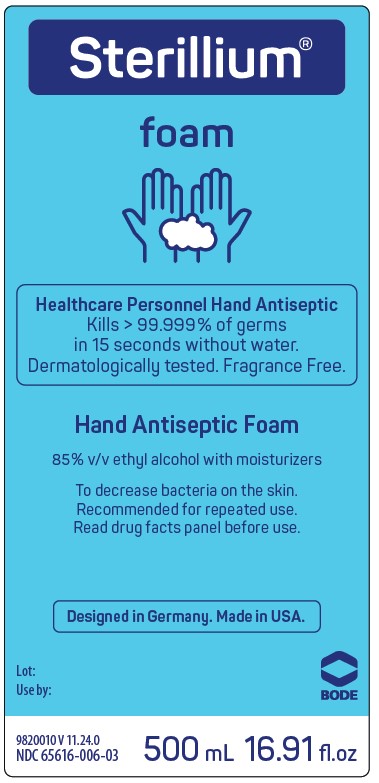 DRUG LABEL: Sterillium Foam
NDC: 65616-006 | Form: LIQUID
Manufacturer: BODE Chemie GmbH
Category: otc | Type: HUMAN OTC DRUG LABEL
Date: 20251208

ACTIVE INGREDIENTS: ALCOHOL 85 mL/100 mL
INACTIVE INGREDIENTS: BIS-PEG/PPG-20/20 DIMETHICONE; ISOPROPYL ALCOHOL; MYRISTYL ALCOHOL; WATER; CYCLOMETHICONE; GLYCERIN

Sterillium Foam 65616-006

Active ingredient

Ethyl Alcohol 85 % v/v

Purpose

Antiseptic

Uses

- To decrease bacteria on the skin.
- Recommended for repeated use.

Warnings

For external use only.

Flammable, keep away from fire or flame.

Do not use in or near the eyes or on mucous membranes.

In case of contact, rinse thoughly with water.

Stop use and ask a doctor if

- irritation and redness develop
- conditions persists for more than 72 hours

Keep out of reach of children.

If swallowed, get medical help or contact a Poison Control Center right away.

Directions

- Apply to clean, dry hands, covering entire surface, including nails
- Rub until dry
- Supervise children in the use of this product

Inactive ingredients

Bis-PEG/PPG-20/20 Dimethicone, Cyclomethicone, Glycerin, Isopropyl Alcohol, Myristyl Alcohol, Water.

Uses

• To decrease bacteria on the skin.

• Recommended for repeated use.

PACKAGE LABEL

Sterillium

foam

Healthcare Personnel Hand Antiseptic

Kills > 99.999% of germs

in 15 seconds without water.

Dermatologically tested. Fragrance Free

Hand Antiseptic Foam

85% v/v ethyl alcohol with moisturizers

To decrease bacteria on the skin.

Recommended for repeated use.

Read drug facts panel before use.

Designed in Germany. Made in USA.

Lot:

Use by:

BODE

NDC 65616-006-03 500 mL 16.91 fl. oz